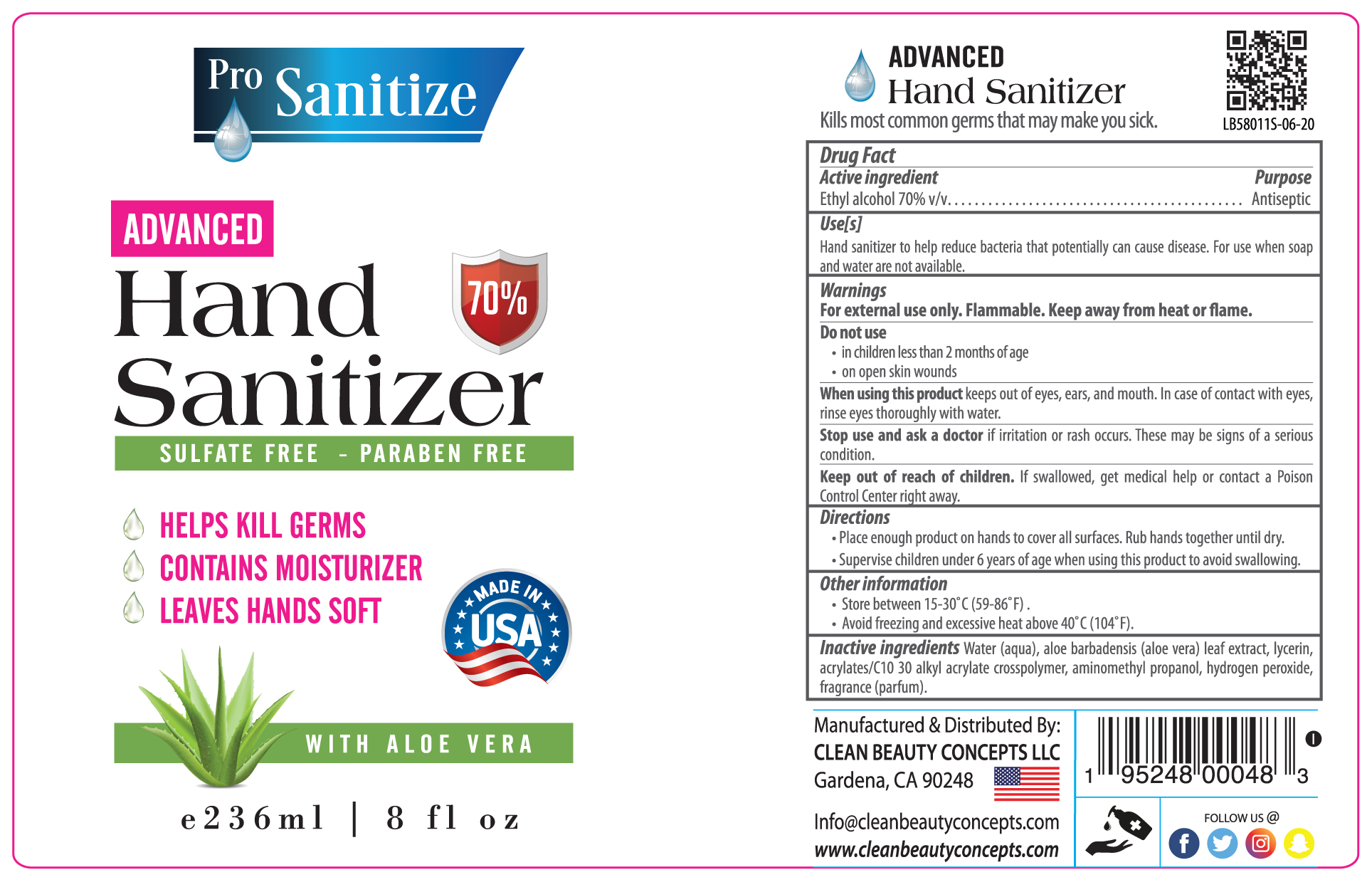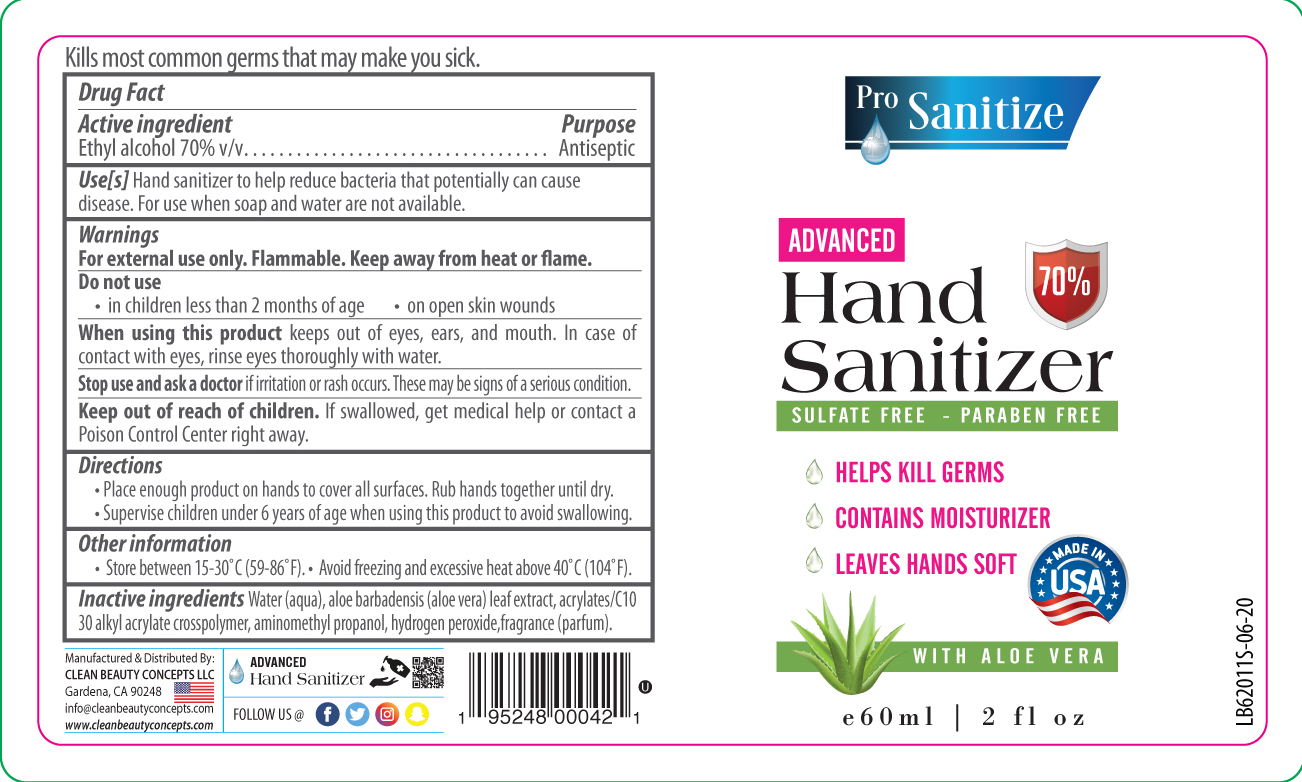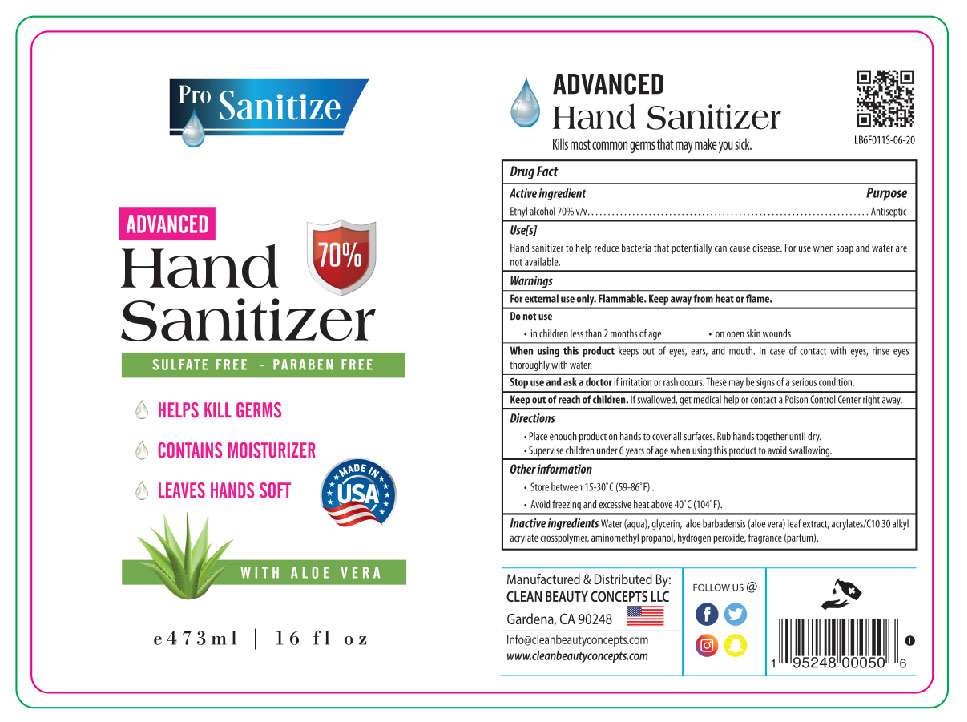 DRUG LABEL: Pro-Sanitize Advanced  with Aloe Vera
NDC: 76665-004 | Form: LIQUID
Manufacturer: Clean Beauty Concepts
Category: otc | Type: HUMAN OTC DRUG LABEL
Date: 20200625

ACTIVE INGREDIENTS: ALCOHOL 70 mL/100 mL
INACTIVE INGREDIENTS: CARBOMER INTERPOLYMER TYPE A (ALLYL SUCROSE CROSSLINKED) 0.2 mL/100 mL; EUCALYPTUS OIL 0.3 mL/100 mL; GLYCERIN 1.45 mL/100 mL; HYDROGEN PEROXIDE 0.125 mL/100 mL; WATER 27.465 mL/100 mL; AMINOMETHYLPROPANOL 0.06 mL/100 mL; ALOE VERA LEAF 0.4 mL/100 mL

The hand sanitizer is manufactured using only the following United States Pharmacopoeia (USP) grade ingredients:

1. Alcohol (ethanol) (USP or Food Chemical Codex (FCC) grade) (70%, volume/volume (v/v)) in an aqueous solution denatured according to Alcohol and Tobacco Tax and Trade Bureau regulations in 27 CFR part 20.
2. Glycerol (1.45% v/v).
3. Hydrogen peroxide (0.125% v/v).
4. Sterile distilled water or boiled cold water. (27.465%)
5. Acrylates/C10 30 Alkyl acrylate crosspolymer(.20% v/v)
6. Aminomethyl propanol (.06% v/v)
7. Fragrance (Parfum) (.3% v/v)
8. Aloe vera lead extract (0.4%)

Active Ingredient(s)

Alcohol 70% v/v. Purpose: Antiseptic

Purpose

Antiseptic

Use

Hand Sanitizer to help reduce bacteria that potentially can cause disease. For use when soap and water are not available.

Warnings

For external use only. Flammable. Keep away from heat or flame

Do not use

- in children less than 2 months of age
- on open skin wounds

When using this product keep out of eyes, ears, and mouth. In case of contact with eyes, rinse eyes thoroughly with water.
Stop use and ask a doctor if irritation or rash occurs. These may be signs of a serious condition.
Keep out of reach of children. If swallowed, get medical help or contact a Poison Control Center right away.

Stop use and ask a doctor if irritation or rash occurs. These may be signs of a serious condition.

Keep out of reach of children. If swallowed, get medical help or contact a Poison Control Center right away.

Directions

- Place enough product on hands to cover all surfaces. Rub hands together until dry.
- Supervise children under 6 years of age when using this product to avoid swallowing.

Other information

- Store between 15-30C (59-86F)
- Avoid freezing and excessive heat above 40C (104F)

Inactive ingredients

water(aqua), glycerin, acrylates/C10 30 alkyl acrylate crosspolymer, aminomethyl propanol, hydrogen peroxide, fragrance(parfum), Aloe Barbadensis

Package Label - Principal Display Panel

473 mL NDC: 76665-004-16

60 mL NDC: 76665-004-02

236 mL NDC: 76665-004-08